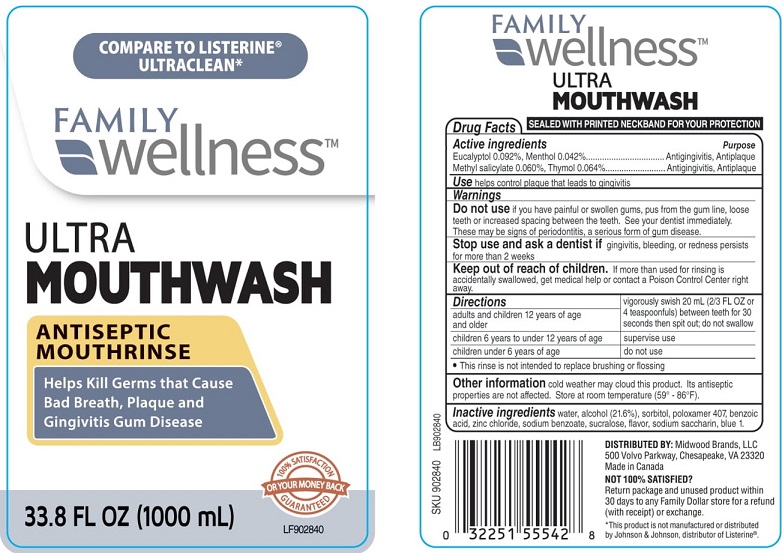 DRUG LABEL: Family Wellness
NDC: 55319-319 | Form: MOUTHWASH
Manufacturer: Family Dollar Services Inc.
Category: otc | Type: HUMAN OTC DRUG LABEL
Date: 20210823

ACTIVE INGREDIENTS: MENTHOL, UNSPECIFIED FORM 0.42 mg/1 mL; THYMOL 0.64 mg/1 mL; EUCALYPTOL 0.92 mg/1 mL; METHYL SALICYLATE 0.6 mg/1 mL
INACTIVE INGREDIENTS: BENZOIC ACID; SORBITOL; SUCRALOSE; POLOXAMER 407; WATER; ALCOHOL; SODIUM BENZOATE; SACCHARIN SODIUM; FD&C BLUE NO. 1; ZINC CHLORIDE

Family Wellness Ultra Mouthrinse, Arctic Mint

Drug Facts

Active ingredients
Eucalyptol 0.092%, Menthol 0.042%

Methyl salicylate 0.060%, Thymol 0.064%

Purpose

Antigingivitis, Antiplaque

Antigingivitis, Antiplaque

INDICATIONS AND USAGE

Use helps control plaque that leads to gingivitis

Warnings

Do not use if you have painful or swollen gums, pus from the gum line, loose teeth or increased spacing between the teeth. See your dentist immediately. These may be signs of periodonititis, a serious form of gum disease.

Stop use and ask a dentist if gingivitis, bleeding, or redness persists for more than 2 weeks

Keep out of reach of children. If more than used for rinsing is accidentally swallowed, get medical help or contact a Poison Control Center right away.

Directions

adults and children 12 years of age and older | vigorously swish 20 mL (2/3 FL OZ or 4 teaspoonfuls) between teeth for 30 seconds then spit out; do not swallow
children 6 years to under 12 years of age | supervise use
children under 6 years | do not use

- This rinse is not intended to replace brushing or flossing

Other information cold weather may cloud this product. Its antiseptic properties are not affected . Store at room temperature (59° - 86°F)

INACTIVE INGREDIENT

Inactive ingredients water, alcohol 21.6%, sorbitol, poloxamer 407, benzoic acid, zinc chloride, sodium benzoate, sucralose, flavor, sodium saccharin, blue 1.

DISTRIBUTED BY: Midwood Brands, LLC

500 Volvo Parkway, Chesapeake, VA 23320

Made in Canada

* This product is not manufactured or distributed by Johnson & Johnson, distributor of Listerine®.

PACKAGE LABEL

COMPARE TO LISTERINE® ULTRACLEAN*

FAMILY wellness™

ULTRA

MOUTHWASH

ANTISEPTIC MOUTHRINSE

Helps Kill Germs that Cause Bad Breath, Plaque and Gingivitis Gum Disease

3.8 FL OZ (1000 mL)